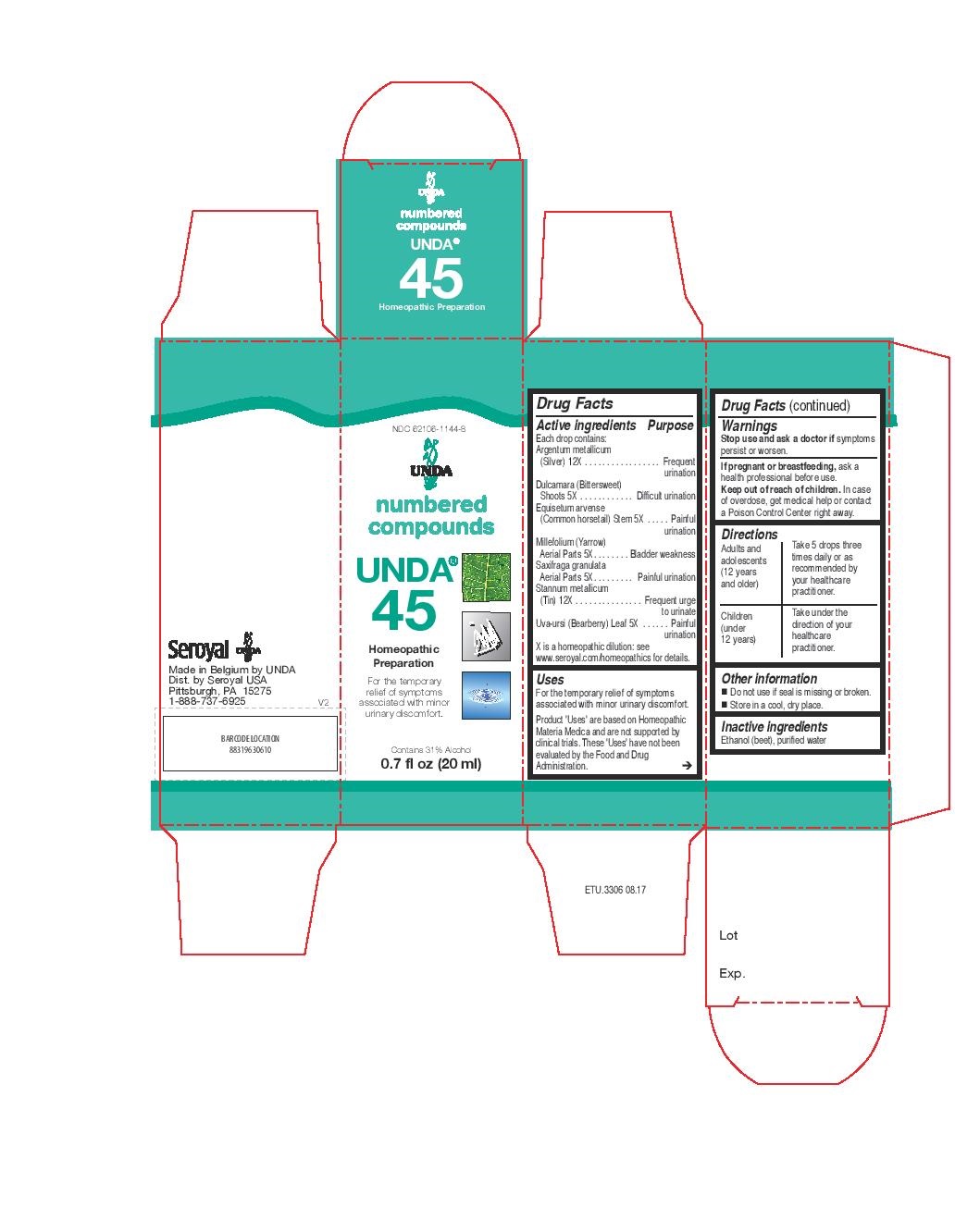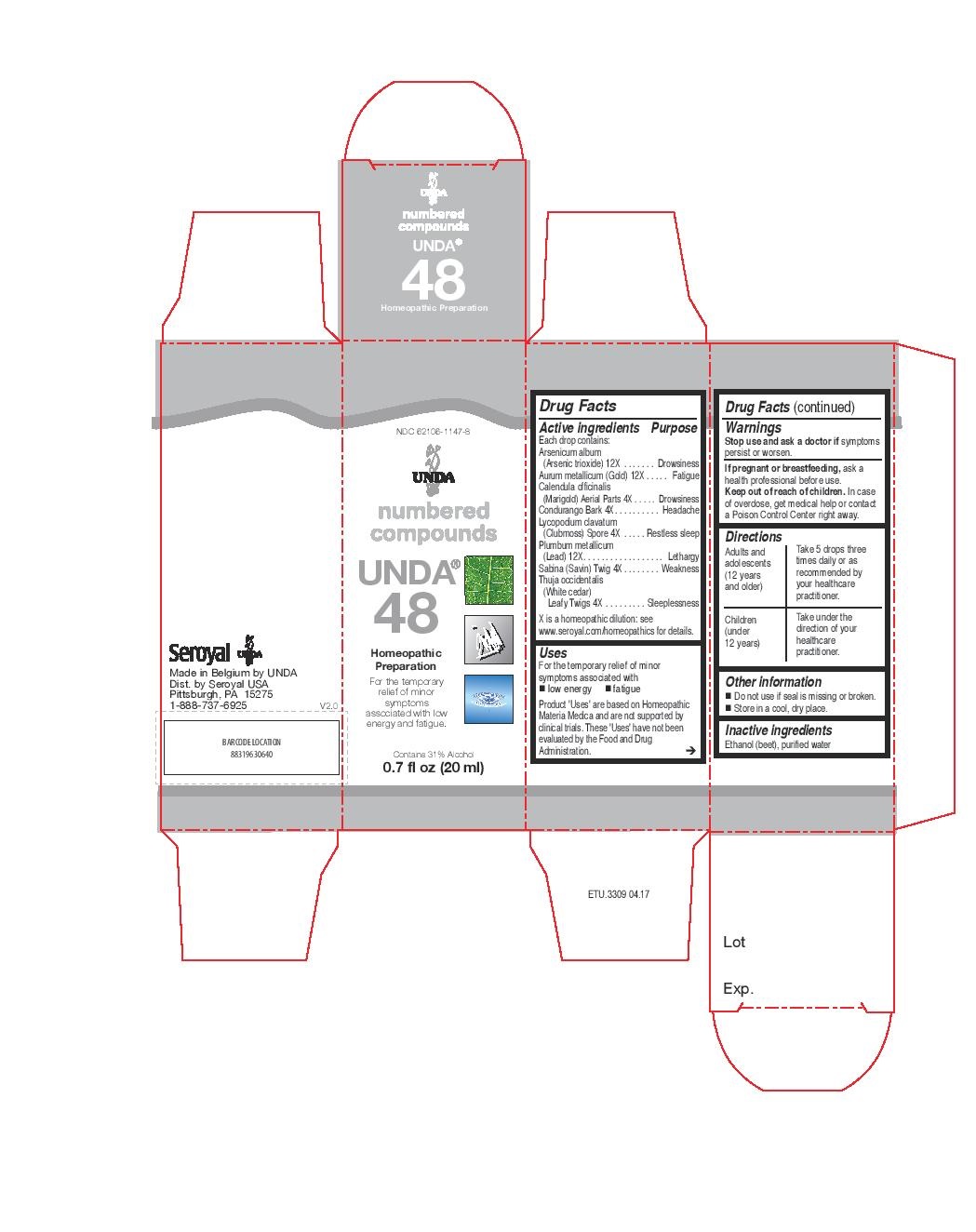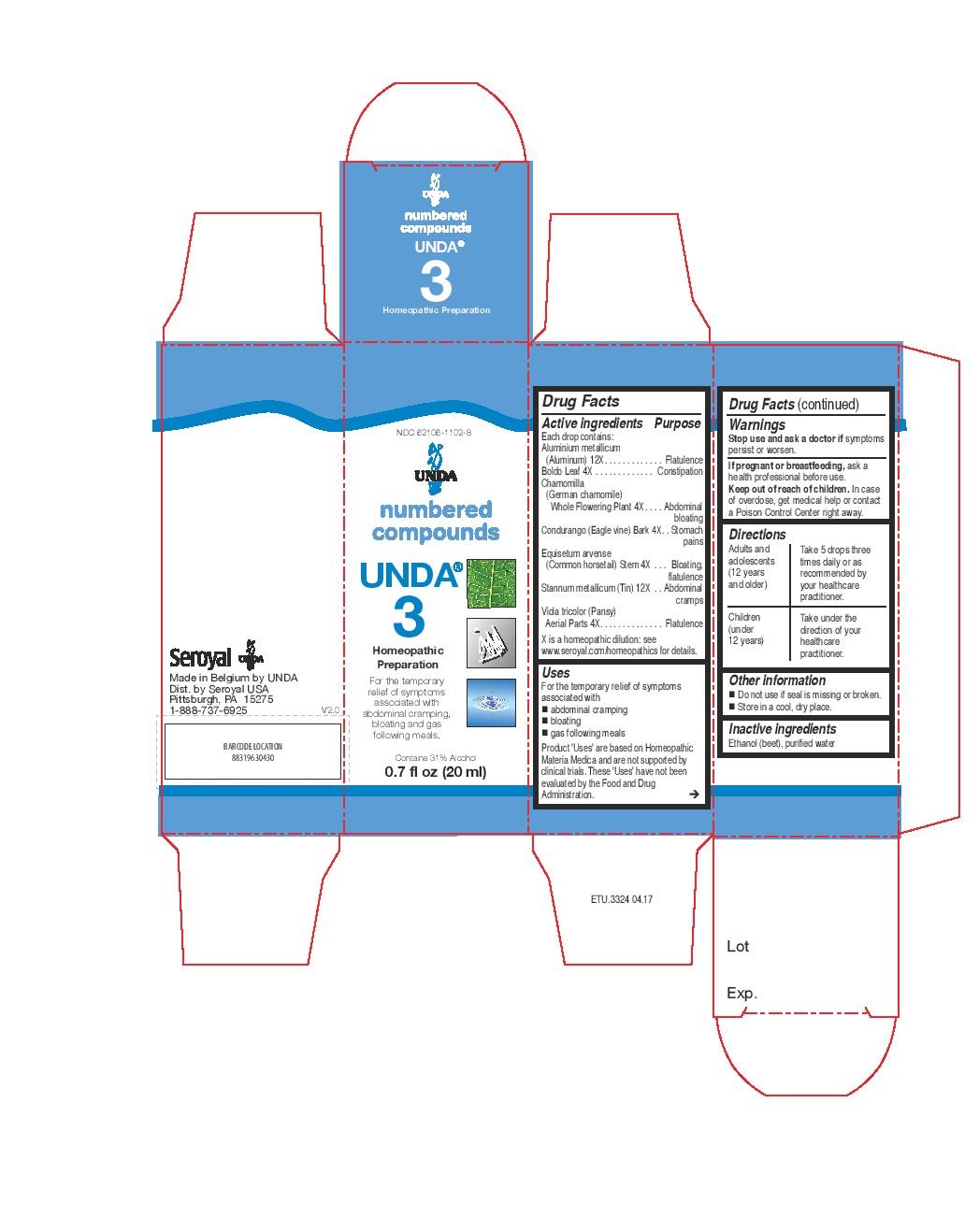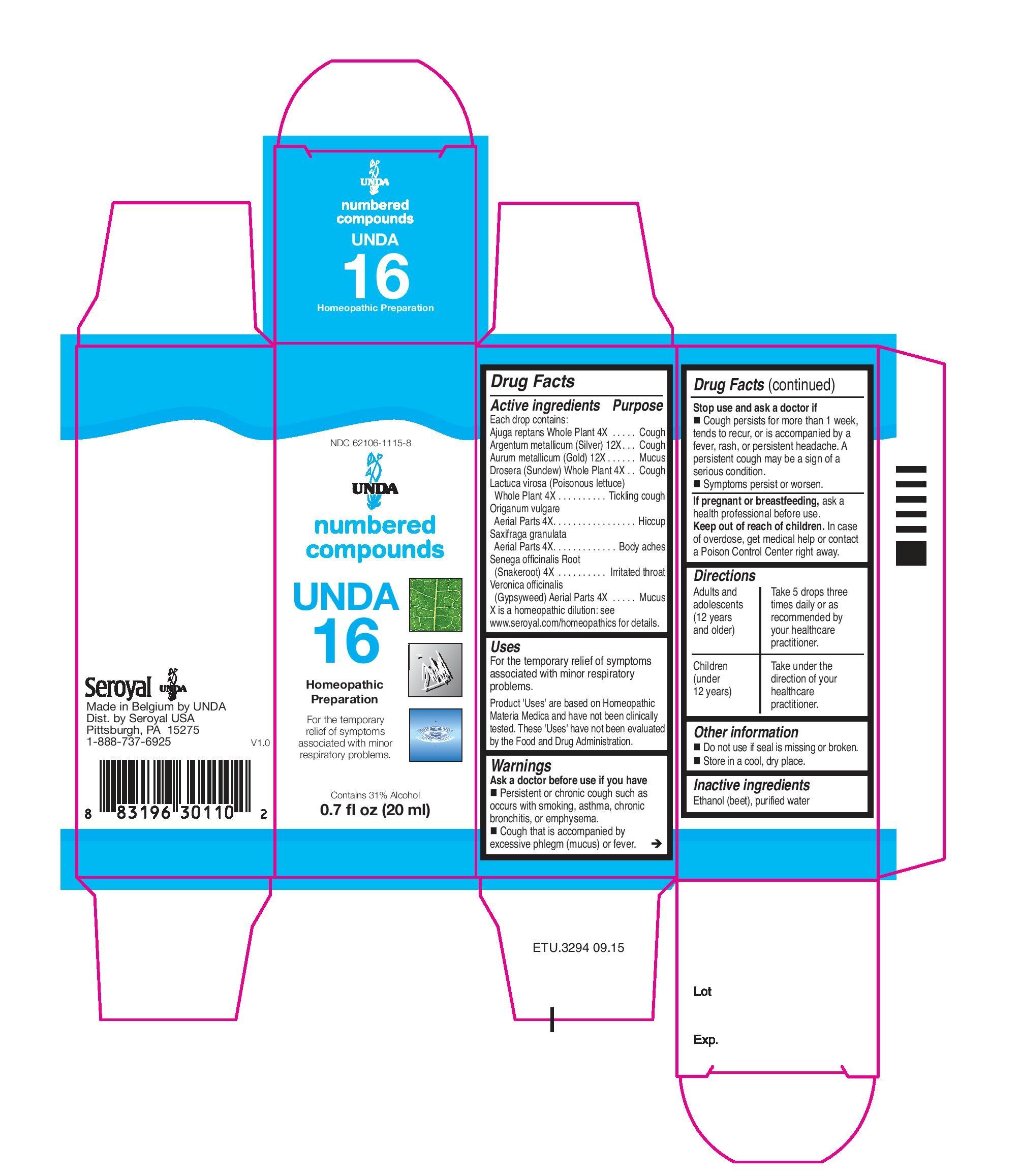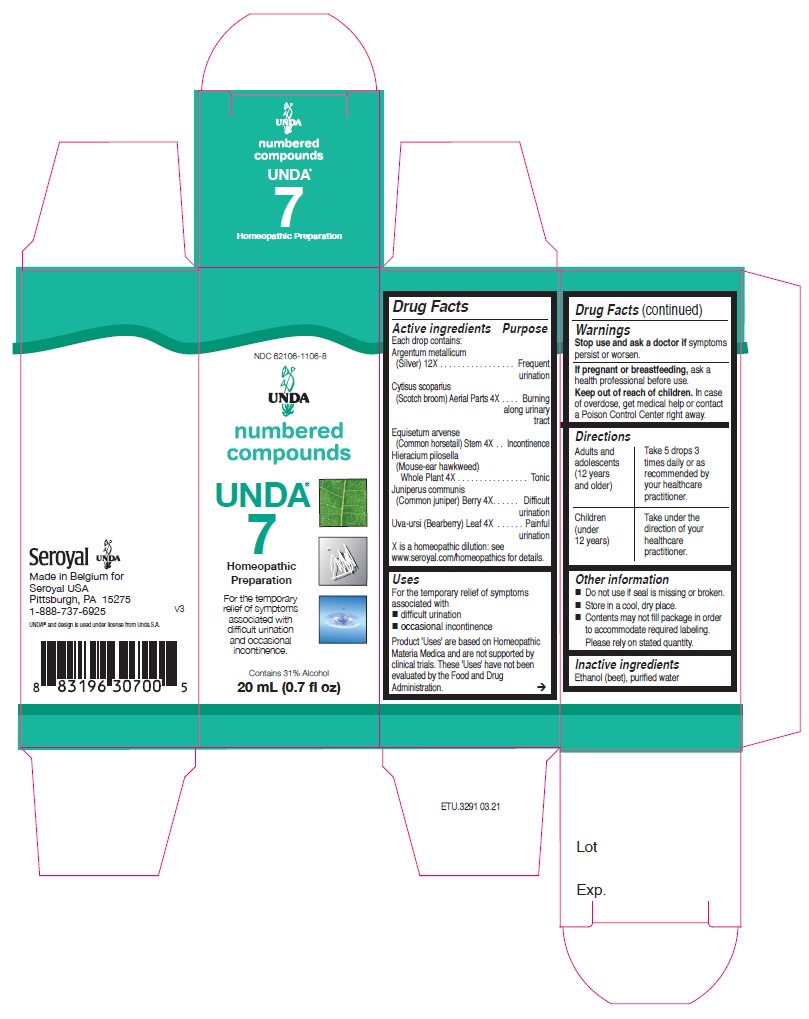 DRUG LABEL: Unda 16
NDC: 62106-1115 | Form: LIQUID
Manufacturer: Seroyal USA
Category: homeopathic | Type: HUMAN OTC DRUG LABEL
Date: 20210715

ACTIVE INGREDIENTS: VERONICA OFFICINALIS FLOWERING TOP 4 [hp_X]/20 mL; AJUGA REPTANS WHOLE 4 [hp_X]/20 mL; DROSERA ROTUNDIFOLIA FLOWERING TOP 4 [hp_X]/20 mL; POLYGALA SENEGA ROOT 4 [hp_X]/20 mL; GOLD 12 [hp_X]/20 mL; SAXIFRAGA GRANULATA WHOLE 4 [hp_X]/20 mL; ORIGANUM VULGARE SUBSP. HIRTUM WHOLE 4 [hp_X]/20 mL; LACTUCA VIROSA 4 [hp_X]/20 mL; SILVER 12 [hp_X]/20 mL
INACTIVE INGREDIENTS: ALCOHOL; WATER

UNDA numbers

Active ingredients
Each drop contains:
Aluminium metallicum (Aluminum) 12X
Boldo Leaf 4X
Chamomilla (German chamomile) Whole Flowering Plant 4X
Condurango (Eagle vine) Bark 4X
Equisetum arvense (Common horsetail) Stem 4X
Stannum metallicum (Tin) 12X
Viola tricolor (Pansy) Aerial Parts 4X

Warnings
Stop use and ask a doctor if symptoms
persist or worsen.
If pregnant or breastfeeding, ask a
health professional before use.
Keep out of reach of children. In case
of overdose, get medical help or contact
a Poison Control Center right away.

Uses

For the temporary relief of symptoms associated with abdominal cramping, bloating and gas following meals.

PREGNANCY OR BREAST FEEDING

If pregnant or breastfeeding, ask a health professional before use.

Keep out of reach of children.

OVERDOSAGE

In case of overdose,get medical help or contact a

Poison Control Center right away.

Stop use and ask a doctor if symptoms
persist or worsen.

Inactive Ingredients:

Ethanol (beet),
purified water

Directions
Adults and adolescents (12 years and older)

Take 5 drops three times daily or as recommended by your healthcare practitioner.

Children (under 12 years)

Take under the direction of your healthcare practitioner.

Uses
For the temporary relief of symptoms associated with abdominal cramping, bloating and gas following meals.

Directions
Adults and adolescents (12 years and older)

Take 5 drops three times daily or as recommended by your healthcare practitioner.

Children (under 12 years)

Take under the direction of your healthcare practitioner.

Active ingredients
Each drop contains:
Argentum metallicum (Silver) 12X
Cytisus scoparius (Scotch broom) Aerial Parts 4X
Equisetum arvense (Common horsetail) Stem 4X
Hieracium pilosella (Mouse-ear hawkweed) Whole Plant 4X
Juniperus communis (Common juniper) Berry 4X
Uva-ursi (Bearberry) Leaf 4X

Uses

For the temporary relief of symptoms
associated with difficult urination
and occasional incontinence.

Warnings

Stop use and ask a doctor if symptoms persist or worsen.
If pregnant or breastfeeding, ask a health professional before use.

Keep out of reach of children.

In case of overdose, get medical help or contact a
Poison Control Center right away.

PREGNANCY OR BREAST FEEDING

If pregnant or breastfeeding, ask a health professional before use.

Keep out of reach of children.

OVERDOSAGE

In case of overdose, get medical help or contact a
Poison Control Center right away.

ASK DOCTOR

If symptoms persist or worsen, consult your healthcare practitioner.

Inactive Ingredients:

Ethanol (beet),
purified water

Directions

Adults and adolescents (12 years and older)

Take 5 drops three times daily or as recommended by your healthcare practitioner.

Children (under 12 years)

Take under the direction of your healthcare practitioner.

Uses

For the temporary relief of symptoms
associated with difficult urination
and occasional incontinence.

Directions

Adults and adolescents (12 years and older)

Take 5 drops three times daily or as recommended by your healthcare practitioner.

Children (under 12 years)

Take under the direction of your healthcare practitioner.

Active ingredients

Each drop contains:
Saxifraga granulata Aerial Parts. 4X
Origanum vulgare Aerial Parts. 4X
Lactuca virosa (Poisonous lettuce) Whole Plant . 4X
Veronica officinalis (Gypsyweed) Aerial Parts . 4X
Ajuga reptansWhole Plant. 4X
Drosera (Sundew)Whole Plant . 4X
Senega officinalis Root . 4X
Aurum metallicum (Gold) . 12X
Argentum metallicum (Silver) . 12X

PURPOSE

Indications
To help with calcium absorption and for symptoms associated
with minor respiratory problems.

Warnings
If pregnant or breastfeeding, ask a health professional before use.

Keep out of reach of children.

In case of overdose, get medical help or contact a
Poison Control Center right away.

If symptoms persist or worsen, consult your healthcare practitioner.

PREGNANCY OR BREAST FEEDING

If pregnant or breastfeeding, ask a health professional before use.

Keep out of reach of children.

OVERDOSAGE

In case of overdose, get medical help or contact a

Poison Control Center right away.

ASK DOCTOR

If symptoms persist or worsen, consult your healthcare practitioner.

Inactive Ingredients:

Ethanol (beet),
purified water

Directions
Adults and adolescents (12 years and older)

Take 5 drops three times daily or as recommended by your healthcare practitioner.

Children (under 12 years)

Take under the direction of your healthcare practitioner.

Indications
To help with calcium absorption and for symptoms associated
with minor respiratory problems.

Directions
Adults and adolescents (12 years and older)

Take 5 drops three times daily or as recommended by your healthcare practitioner.

Children (under 12 years)

Take under the direction of your healthcare practitioner.

Active ingredients
Each drop contains:
Argentum metallicum (Silver) 12X
Dulcamara (Bittersweet) Shoots 5X
Equisetum arvense (Common horsetail) Stem 5X
Millefolium (Yarrow) Aerial Parts 5X
Saxifraga granulata Aerial Parts 5X
Stannum metallicum (Tin) 12X
Uva-ursi (Bearberry) Leaf 5X

Uses
For the temporary relief of symptoms
associated with minor urinary discomfort.

Warnings
Stop use and ask a doctor if symptoms persist or worsen.

If pregnant or breastfeeding, ask a health professional before use.
Keep out of reach of children. In case of overdose, get medical help or contact
a Poison Control Center right away.

PREGNANCY OR BREAST FEEDING

If pregnant or breastfeeding, ask a health professional before use.

Keep out of reach of children.

OVERDOSAGE

In case of overdose, get medical help or contact a

Poison Control Center right away.

Stop use and ask a doctor if symptoms persist or worsen.

Other information
Do not use if seal is missing or broken.

Store in a cool, dry place.

Contents may not fill package in order
to accommodate required labeling.
Please rely on stated quantity.

Inactive Ingredients:

Ethanol (beet),
purified water

Directions

Adults and adolescents (12 years and older)

Take 5 drops three times daily or as recommended by your healthcare practitioner.

Children (under 12 years)

Take under the direction of your healthcare practitioner.

Uses
For the temporary relief of symptoms associated with minor urinary discomfort.

Directions

Adults and adolescents (12 years and older)

Take 5 drops three times daily or as recommended by your healthcare practitioner.

Children (under 12 years)

Take under the direction of your healthcare practitioner.

Active ingredients
Each drop contains:
Arsenicum album (Arsenic trioxide) 12X
Aurum metallicum (Gold) 12X
Calendula officinalis (Marigold) Aerial Parts 4X
Condurango Bark 4X
Lycopodium clavatum (Clubmoss) Spore 4X
Plumbum metallicum (Lead) 12X
Sabina (Savin) Twig 4X
Thuja occidentalis (White cedar) Leafy Twigs 4X

Uses
For the temporary relief of minor symptoms associated with low energy and fatigue.

Warnings
Stop use and ask a doctor if symptoms persist or worsen.
If pregnant or breastfeeding, ask a health professional before use.
Keep out of reach of children.

In case of overdose, get medical help or contact a Poison Control Center right away.

PREGNANCY OR BREAST FEEDING

If pregnant or breastfeeding, ask a health professional before use.

Keep out of reach of children.

OVERDOSAGE

In case of overdose, get medical help or contact a
Poison Control Center right away.

Stop use and ask a doctor if symptoms persist or worsen.

Inactive Ingredients:

Ethanol (beet),
purified water

Directions
Adults and adolescents (12 years and older)

Take 5 drops three times daily or as recommended by your healthcare practitioner.

Children (under 12 years)

Take under the direction of your healthcare practitioner.

Uses
For the temporary relief of minor symptoms associated with low energy and fatigue.

Directions
Adults and adolescents (12 years and older)

Take 5 drops three times daily or as recommended by your healthcare practitioner

Children (under 12 years)

Take under the direction of your healthcare practitioner.

PACKAGE LABEL

NDC 62106-1102-8

UNDA

numbered compounds

UNDA 3

Homeopathic Preparation

For the temporary relief of symptoms associated with abdominal cramping, bloating and gas following meals.

Contains 31% Alcohol
0.7 fl oz (20 ml)

PACKAGE LABEL

NDC 62106-1106-8

UNDA

numbered compounds

UNDA 7

Homeopathic Preparation

For the temporary
relief of symptoms
associated with
difficult urination
and occasional
incontinence.

Contains 31% Alcohol
0.7 fl oz (20 ml)

PACKAGE LABEL

UNDA

numbered compounds

NDC 62106-1115-8

Unda 16

Homeopathic Preparation

For the temporary relief of symptoms associated with minor respiratory problems.

Contains 31% Alcohol
0.7 fl oz (20 ml)

PACKAGE LABEL

NDC 62106-1144-8

UNDA

numbered compounds

UNDA 45

Homeopathic Preparation

For the temporary relief of symptoms
associated with minor urinary discomfort.

Contains 31% Alcohol
0.7 fl oz (20 ml)

PACKAGE LABEL

NDC 62106-1147-8

UNDA

numbered compounds

UNDA 48

Homeopathic Preparation

For the temporary relief of minor
symptoms associated with low
energy and fatigue.

Contains 31% Alcohol
0.7 fl oz (20 ml)